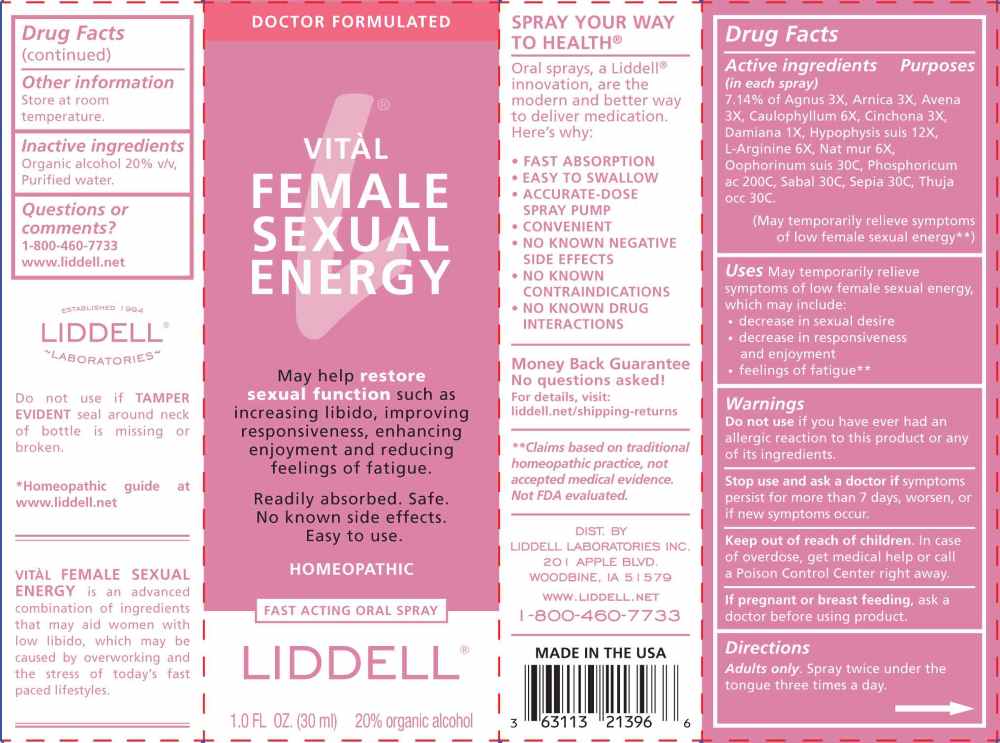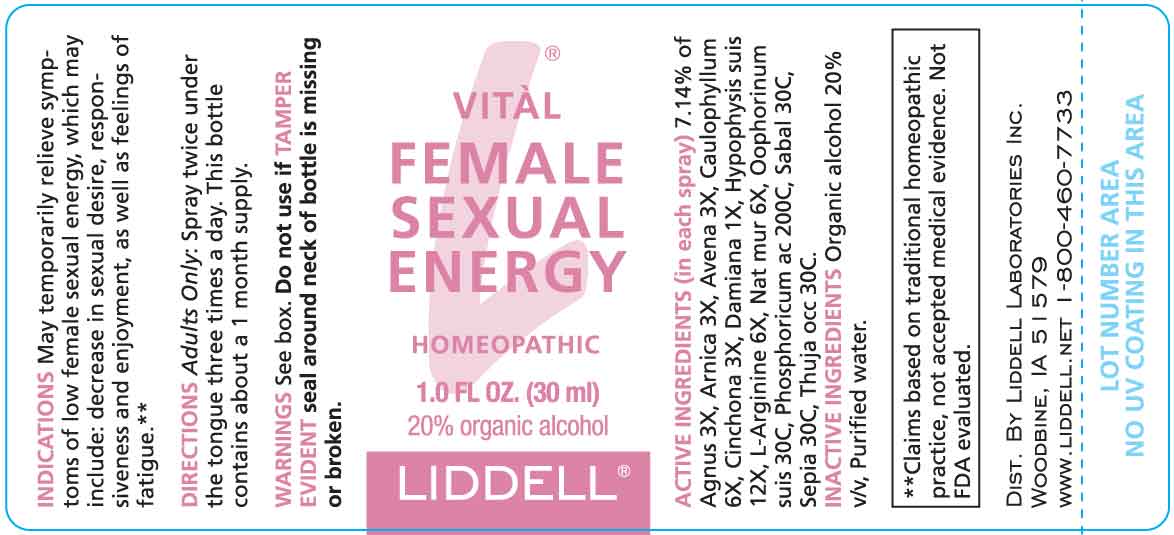 DRUG LABEL: Vital Female Sexual Energy
NDC: 50845-0285 | Form: SPRAY
Manufacturer: Liddell Laboratories, Inc.
Category: homeopathic | Type: HUMAN OTC DRUG LABEL
Date: 20260130

ACTIVE INGREDIENTS: CHASTE TREE FRUIT 3 [hp_X]/1 mL; ARNICA MONTANA WHOLE 3 [hp_X]/1 mL; AVENA SATIVA FLOWERING TOP 3 [hp_X]/1 mL; CAULOPHYLLUM THALICTROIDES ROOT 6 [hp_X]/1 mL; CINCHONA OFFICINALIS BARK 3 [hp_X]/1 mL; TURNERA DIFFUSA LEAFY TWIG 1 [hp_X]/1 mL; SUS SCROFA PITUITARY GLAND 12 [hp_X]/1 mL; ARGININE 6 [hp_Q]/1 mL; SODIUM CHLORIDE 6 [hp_X]/1 mL; SUS SCROFA OVARY 30 [hp_C]/1 mL; PHOSPHORIC ACID 200 [hp_C]/1 mL; SAW PALMETTO 30 [hp_C]/1 mL; SEPIA OFFICINALIS JUICE 30 [hp_C]/1 mL; THUJA OCCIDENTALIS LEAFY TWIG 30 [hp_C]/1 mL
INACTIVE INGREDIENTS: WATER; ALCOHOL

DRUG FACTS:

ACTIVE INGREDIENTS:

(in each spray) 7.14% of Agnus Castus 3X, Arnica Montana 3X, Avena Sativa 3X, Caulophyllum Thalictroides 6X, Cinchona Officinalis 3X, Damiana 1X, Hypophysis Suis 12X, L-Arginine 6X, Natrum Muriaticum 6X, Oophorinum Suis 30C, Phosphoricum Acidum 200C, Sabal Serrulata 30C, Sepia 30C, Thuja Occidentalis 30C.

PURPOSE:

May temporarily relieve symptoms of low female sexual energy, which may include: decrease in sexual desire, responsiveness and enjoyment, as well as feelings of fatigue**

**Claims based on traditional homeopathic practice, not accepted medical evidence. Not FDA evaluated.

WARNINGS:

Do not use if you have ever had an allergic reaction to this product or any of its ingredients.

Stop use and ask a doctor if symptoms persist for more than 7 days, worsen, or if new symptoms occur.

Keep out of reach of children. In case of overdose, get medical help or call a Poison Control Center right away.

If pregnant or breast feeding, ask a health professional before using product.

Do not use if TAMER EVIDENT seal around neck of bottle is missing or broken.

Store at room temperature.

KEEP OUT OF REACH OF CHILDREN:

In case of overdose, get medical help or call a Poison Control Center right away.

DIRECTIONS:

Adults only. Spray twice under the tongue three times a day.

This bottle contains about a 1 month supply.

USES:

May temporarily relieve symptoms of low female sexual energy, which may include:

• decrease in sexual desire
• decrease in responsiveness and enjoyment
• feelings of fatigue**

**Claims based on traditional homeopathic practice, not accepted medical evidence. Not FDA evaluated.

INACTIVE INGREDIENTS:

Organic alcohol 20% v/v, Purified water.

QUESTIONS:

DIST. BY:

LIDDELL LABORATORIES, INC.

201 APPLE BLVD.

WOODBINE, IA 51579

WWW.LIDDELL.NET

1-800-460-7733

PACKAGE LABEL DISPLAY:

DOCTOR FORMULATED

VITAL FEMALE SEXUAL ENERGY

May help restore sexual function such as
increasing libido, improving responsiveness,
enhancement enjoyment and reducing feelings of fatigue.

Readily absorbed. Safe.
No known side effects.

Easy to use.

HOMEOPATHIC

FAST ACTING ORAL SPRAY

LIDDELL

1.0 FL OZ (30 ml)